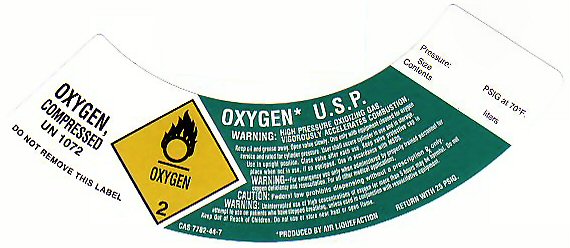 DRUG LABEL: OXYGEN
NDC: 42809-0002 | Form: GAS
Manufacturer: Express Medical Inc
Category: prescription | Type: HUMAN PRESCRIPTION DRUG LABEL
Date: 20251023

ACTIVE INGREDIENTS: OXYGEN 99 L/100 L

PRODUCT WARNINGS AND PRECAUTIONS

WARNING: HIGH PRESSURE OXIDIZING GAS VIGOROUSLY ACCELERATES COMBUSTION. KEEP OIL AND GREASE AWAY. OPEN VALVE SLOWLY. USE ONLY WITH EQUIPMENT CLEANED FOR OXYGEN SERVICE AND RATED FOR CYLINDER PRESSURE. USER SHALL SECURE CYLINDER IN USE AND IN STORAGE. USE IN UPRIGHT POSITION. CLOSE VALVE AFTER EACH USE AND WHEN EMPTY. KEEP VALVE PROTECTIVE CAP IN PLACE WHEN NOT IN USE IF SO EQUIPPED. USE IN ACCORDANCE WITH MSDS.

WARNING: UNINTERRUPTED USE OF HIGH CONCENTRATIONS OF OXYGEN FOR MORE THAN 5 HOURS MAY BE HARMFUL. DO NOT ATTEMPT TO USE ON PATIENTS WHO HAVE STOPPED BREATHING UNLESS USED IN CONJUNCTION WITH RESUSCITATIVE EQUIPMENT. KEEP OUT OF REACH OF CHILDREN. DO NOT USE OR STORE NEAR HEAT OR OPEN FLAME. RETURN WITH 25 PSIG.

OXYGEN COMPRESSED LABEL

OXYGEN COMPRESSED UN 1072 OXYGEN U.S.P. OXYGEN-2
WARNING: FOR EMERGENCY USE ONLY WHEN ADMINISTERED BY PROPERLY TRAINED PERSONNEL FOR OXYGEN DEFICIENCY AND RESUSCITATION. FOR ALL OTHER MEDICAL APPLICATIONS Rx ONLY.
CAUTION: FEDERAL LAW PROHIBITS DISPENSING WITHOUT A PRESCRIPTION. Rx ONLY. PRODUCED BY AIR LIQUEFACTION
CAS 7782-44-7 PRESSURE:_____ PSIG AT 70 F SIZE_______ CONTENTS__________LITERS